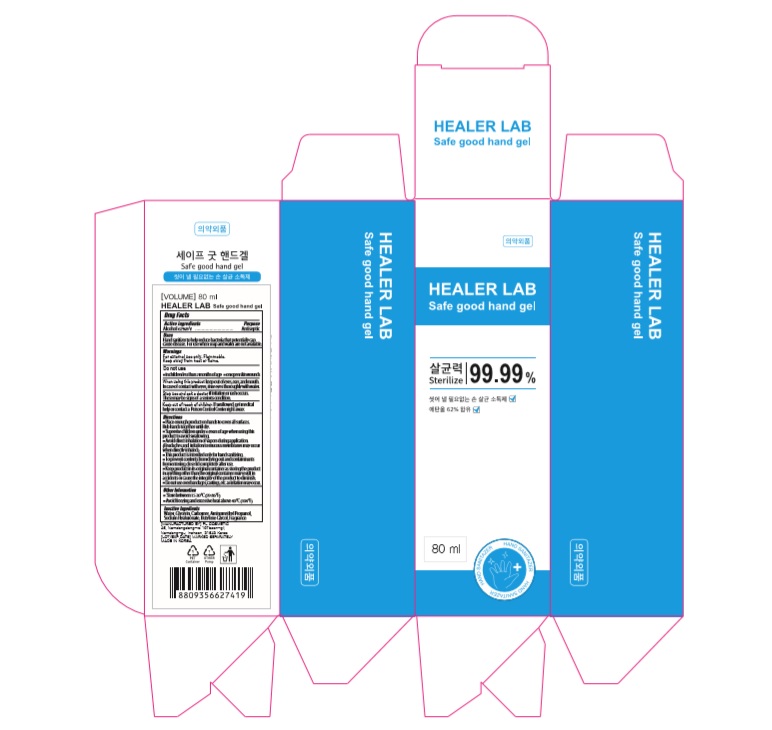 DRUG LABEL: HEALER LAB Safe good hand gel
NDC: 74339-0080 | Form: SPRAY
Manufacturer: PL COSMETIC
Category: otc | Type: HUMAN OTC DRUG LABEL
Date: 20200415

ACTIVE INGREDIENTS: ALCOHOL 49.6 mL/80 mL
INACTIVE INGREDIENTS: GLYCERIN; CARBOMER HOMOPOLYMER, UNSPECIFIED TYPE; WATER; BUTYLENE GLYCOL; HYALURONATE SODIUM; AMINOMETHYLPROPANOL

[HEALER LAB SAFE GOOD HAND Gel] 80 ml : 74339-0080-2